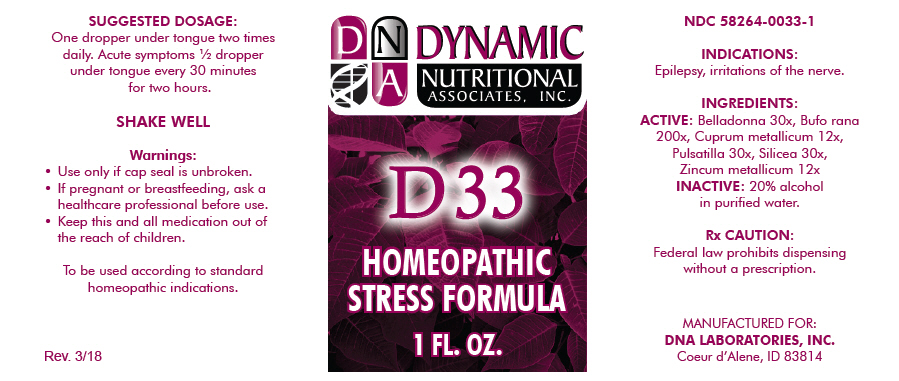 DRUG LABEL: D-33
NDC: 58264-0033 | Form: SOLUTION
Manufacturer: DNA Labs, Inc.
Category: homeopathic | Type: HUMAN OTC DRUG LABEL
Date: 20250113

ACTIVE INGREDIENTS: ATROPA BELLADONNA 30 [hp_X]/1 mL; BUFO BUFO CUTANEOUS GLAND 200 [hp_X]/1 mL; COPPER 12 [hp_X]/1 mL; ANEMONE PRATENSIS 30 [hp_X]/1 mL; SILICON DIOXIDE 30 [hp_X]/1 mL; ZINC 12 [hp_X]/1 mL
INACTIVE INGREDIENTS: ALCOHOL; WATER

D-33

NDC 58264-0033-1

INDICATIONS

PURPOSE

Epilepsy, irritations of the nerve.

INGREDIENTS

ACTIVE

Belladonna 30x, Bufo rana 200x, Cuprum metallicum 12x, Pulsatilla 30x, Silicea 30x, Zincum metallicum 12x

INACTIVE

20% alcohol in purified water.

Rx CAUTION

Federal law prohibits dispensing without a prescription.

SUGGESTED DOSAGE

One dropper under tongue two times daily. Acute symptoms ½ dropper under tongue every 30 minutes for two hours.

STORAGE AND HANDLING

SHAKE WELL

Warnings

- Use only if cap seal is unbroken.

PREGNANCY OR BREAST FEEDING

- If pregnant or breastfeeding, ask a healthcare professional before use.

KEEP OUT OF REACH OF CHILDREN

- Keep this and all medication out of the reach of children.

To be used according to standard homeopathic indications.

PRINCIPAL DISPLAY PANEL - 1 FL. OZ. Bottle Label

DYNAMIC
NUTRITIONAL
ASSOCIATES, INC.

D 33

HOMEOPATHIC
STRESS FORMULA

1 FL. OZ.